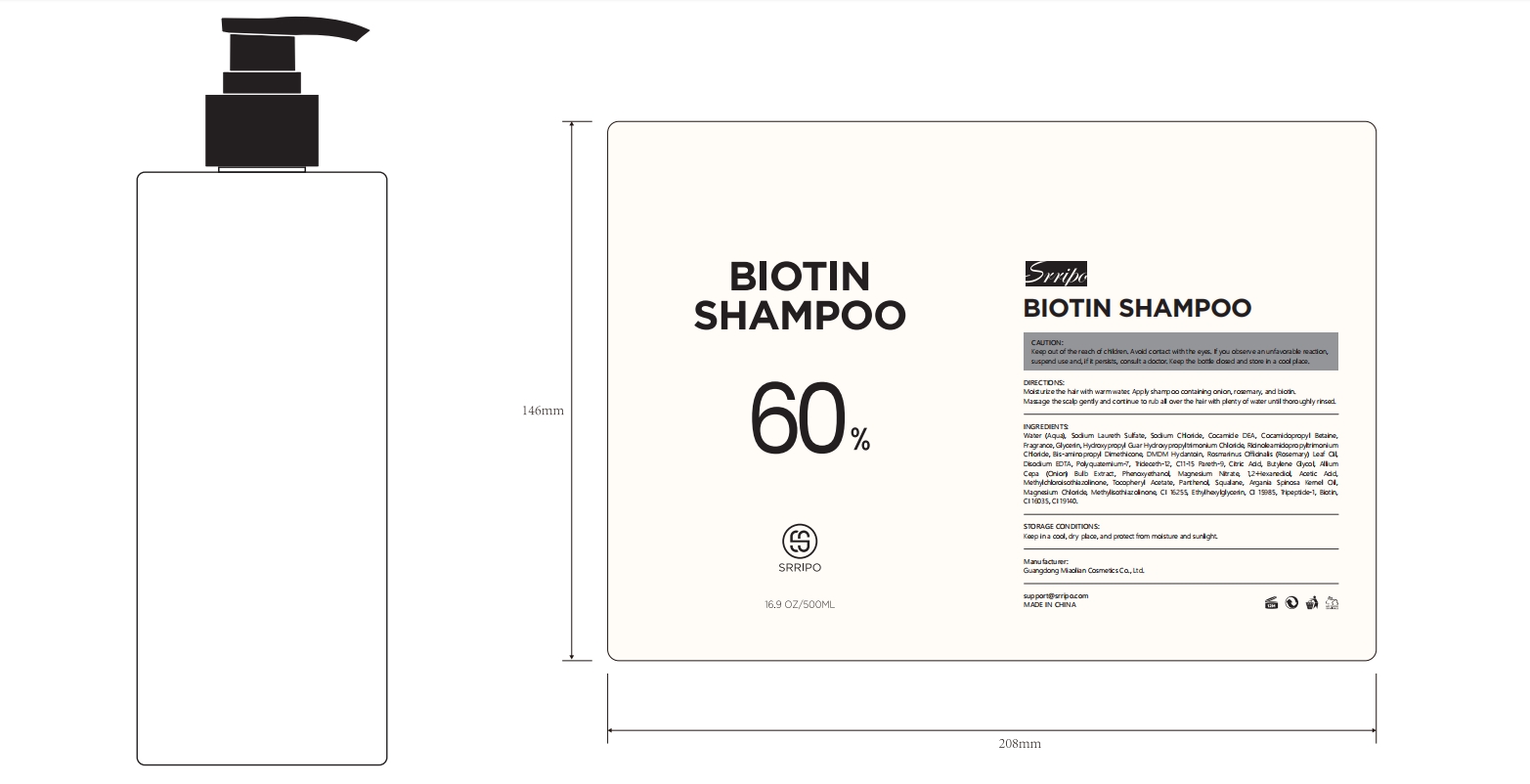 DRUG LABEL: Srripo Biotin Shampoo/
NDC: 84507-021 | Form: SHAMPOO
Manufacturer: Guangdong Miaolian Cosmetics Co., Ltd.
Category: otc | Type: HUMAN OTC DRUG LABEL
Date: 20240911

ACTIVE INGREDIENTS: PROPANEDIOL 0.1 mg/100 mL
INACTIVE INGREDIENTS: WATER

DOSAGE AND ADMINISTRATION

Moisturize the hair with warm water. Apply shampoo containing onion, rosemary, and biotin.Massage the scalp gently and continue to rub all over the hair with plenty of water until thoroughly rinsed.

WARNINGS

Keep in a cool, dry place, and protect from moisture and sunlight.

INACTIVE INGREDIENT

Water....

INDICATIONS AND USAGE

Improves the scalp environment, repairs damaged hair, and moisturizes hair. This product contains plant essences to repair the scalp barrier, provide a non-greasy moisturizing effect, and make hair look full and natural.

KEEP OUT OF REACH OF CHILDREN

Keep out of the reach of children. Avoid contact with the eyes. If you observe an unfavorable reaction, suspend use and, if it persists, consult a doctor. Keep the bottle closed and store in a cool place.

Close

PURPOSE

Improves the scalp environment, repairs damaged hair, and moisturizes hair.